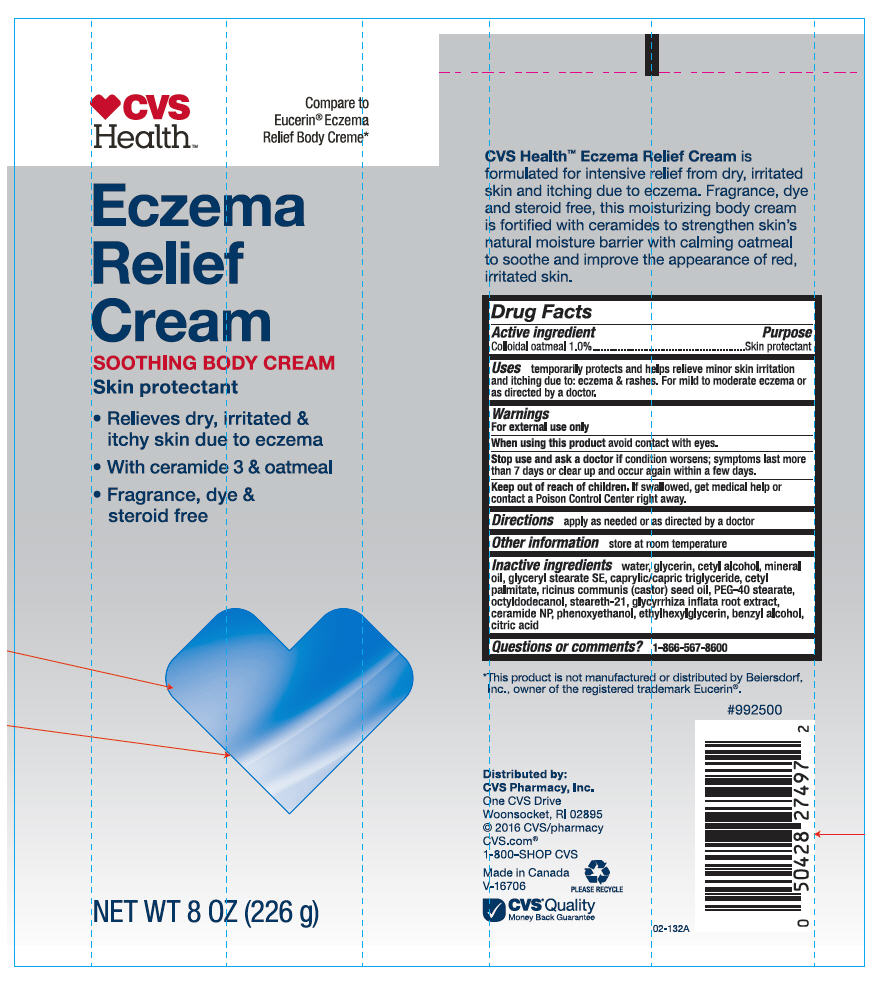 DRUG LABEL: CVS Eczema Relief
NDC: 69842-388 | Form: CREAM
Manufacturer: CVS Health
Category: otc | Type: HUMAN OTC DRUG LABEL
Date: 20241111

ACTIVE INGREDIENTS: Oatmeal 10 mg/1 g
INACTIVE INGREDIENTS: Water; Glycerin; Cetyl Alcohol; Mineral Oil; Glyceryl Stearate SE; Medium-Chain Triglycerides; Cetyl Palmitate; Castor Oil; PEG-40 MONOSTEARATE; Octyldodecanol; Steareth-21; Glycyrrhiza Inflata Root; Ceramide NP; Phenoxyethanol; Ethylhexylglycerin; Benzyl Alcohol; Citric Acid Monohydrate

CVS Eczema Relief Cream
Skin Protectant

Active ingredients

Colloidal Oatmeal 1.0%

Purpose

Skin Protectant

Uses

temporarily protects and helps relieve minor skin irritation and itching due to: eczema & rashes. For mild to moderate eczema or as directed by a doctor.

Warnings

For external use only

When using this product avoid contact with eyes.

Stop use and ask a doctor if condition worsens; symptoms last more than 7 days or clear up and occur again within a few days.

Keep out of reach of children. If swallowed, get medical help or contact a Poison Control Center right away.

Directions

apply as needed or as directed by a doctor

Other information

Store at room temperature

Inactive ingredients

Water, Glycerin, Cetyl Alcohol, Mineral Oil, Glyceryl Stearate SE, Caprylic/Capric Triglyceride, Cetyl Palmitate, Ricinus Communis (Castor) Seed Oil, PEG-40 Stearate, Octyldodecanol, Steareth-21, Glycyrrhiza Inflata Root Extract, Ceramide NP, Phenoxyethanol, Etylhexylglycerin, Benzyl Alcohol, Citric Acid.

Questions or comments?

1-866-567-8600

Distributed by:
CVS Pharmacy, Inc.
One CVS Drive
Woonsocket, RI 02895

PRINCIPAL DISPLAY PANEL - 226 g Tube Label

♥CVS
Health™

Compare to
Eucerin® Eczema
Relief Body Creme*

Eczema
Relief
Cream

SOOTHING BODY CREAM
Skin protectant

- Relieves dry, irritated &
  itchy skin due to eczema
- With ceramide 3 & oatmeal
- Fragrance, dye &
  steroid free

NET WT 8 OZ (226 g)